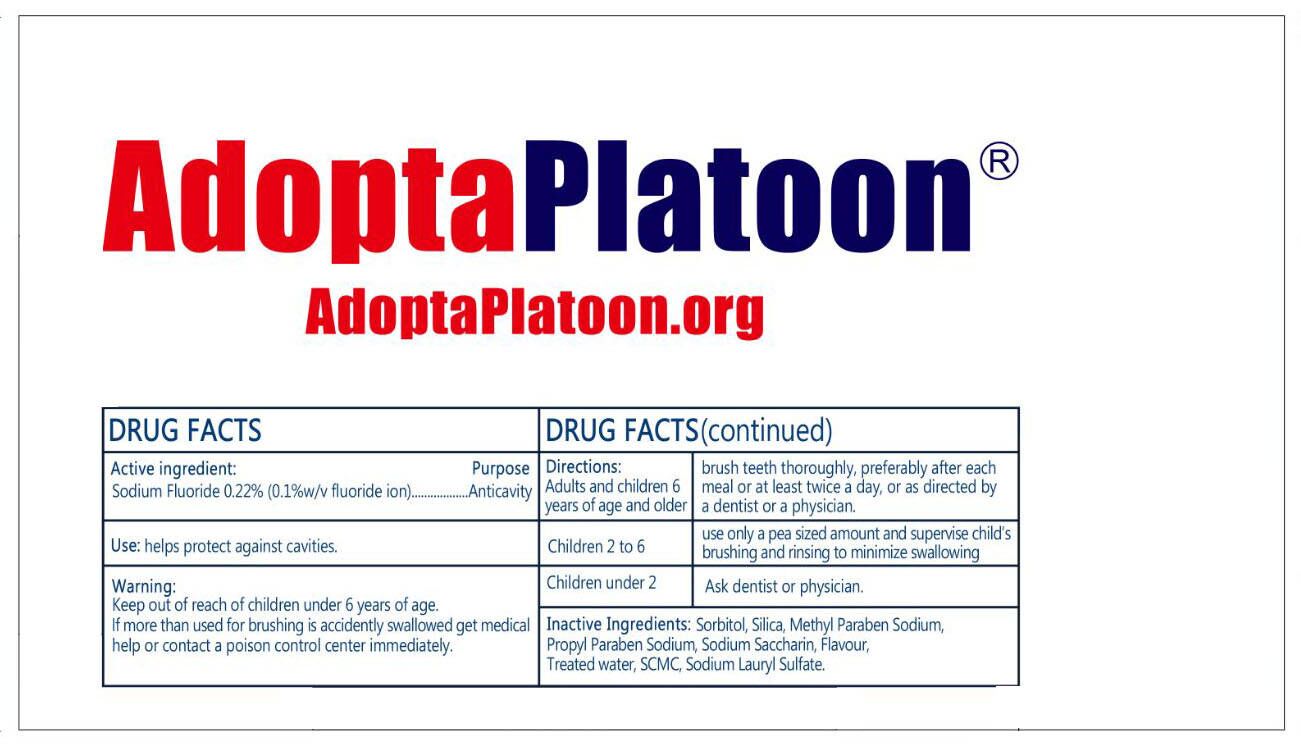 DRUG LABEL: AdoptaPlatoon
NDC: 85162-004 | Form: PASTE, DENTIFRICE
Manufacturer: Yangzhou ONE & ONLY Personal Care Products Co., LTD
Category: otc | Type: HUMAN OTC DRUG LABEL
Date: 20250321

ACTIVE INGREDIENTS: SODIUM FLUORIDE 0.1 g/100 mL
INACTIVE INGREDIENTS: SACCHARIN SODIUM; SORBITOL; METHYLPARABEN SODIUM; HYDRATED SILICA; SODIUM LAURYL SULFATE; PROPYLPARABEN SODIUM; WATER

85162-004 AdoptaPlatoon

Active ingredients

Sodium Fluoride 0.22%(0.1 w/v Fluoride ion)

Purpose

anticavity

Uses

Help protect against dental cavities.

Warnings

Keep out of the reach of children under 6 years of age. If more than used for brushing is accidently swallowed,get medical help or contact a Poison Control Center immediately.

Keep out of reach of children.

Directions

Adult and children six years of age or older:

- Brush teeth thoroughly, preferrably after each meal or at least twice a day, or as directed by a dentist or a physician.

Children 2-6:

- Use only a pea sized amount and supervise children's brushing and rinsing to minimize swallowing.

Children under 2:

- Ask a dentist or physician

INACTIVE INGREDIENT

Sorbitol, Silica,Methyl Paraben Sodium, Propyl Paraben Sodium, Sodium Saccharin, Flavor, Water, SCMC, Sodium Lauryl Sulfate